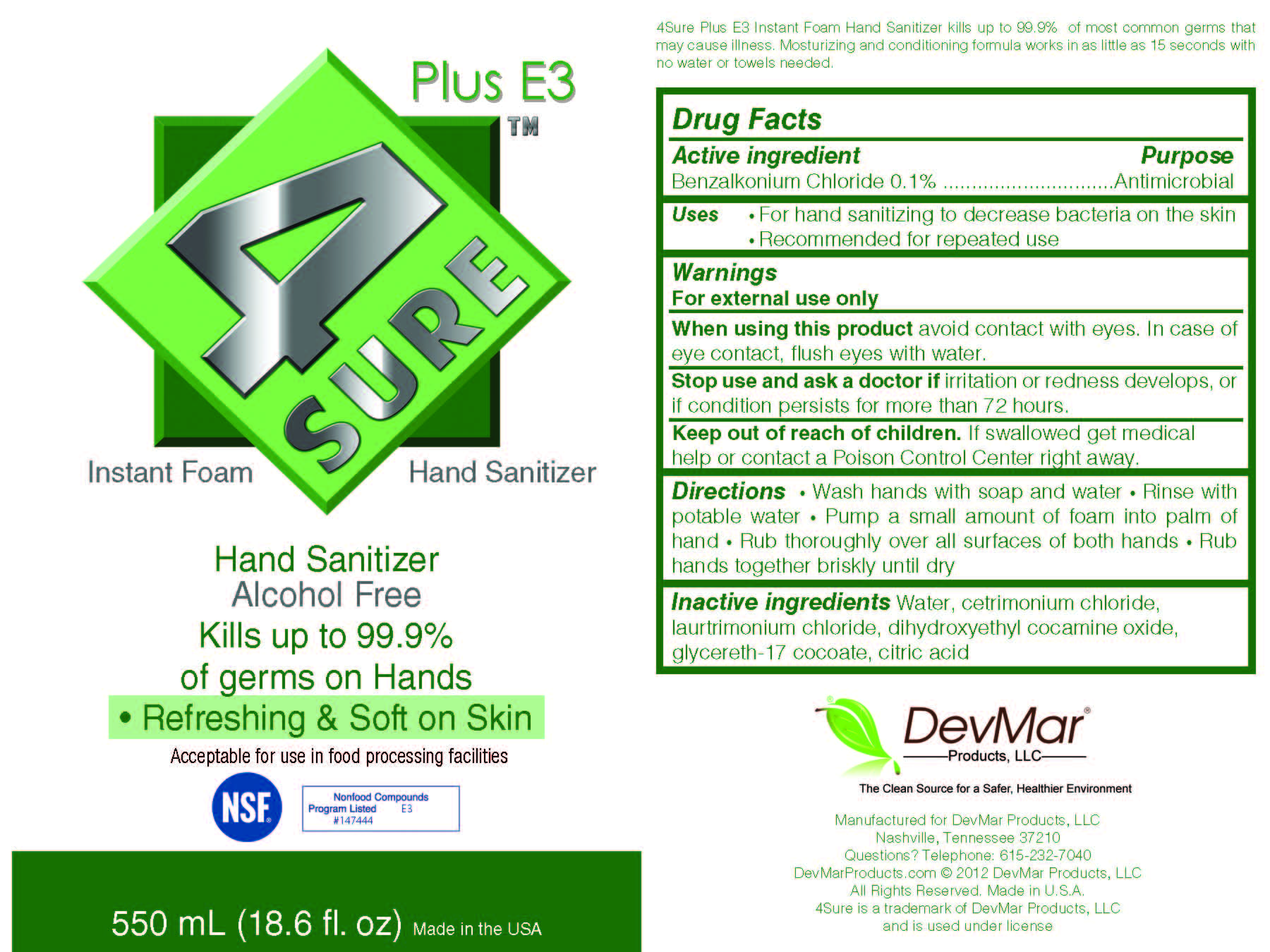 DRUG LABEL: 4 SURE Plus E3 Instant Foam Hand Sanitizer
                
NDC: 54410-001 | Form: LIQUID
Manufacturer: DevMar Products LLC
Category: otc | Type: HUMAN OTC DRUG LABEL
Date: 20130313

ACTIVE INGREDIENTS: BENZALKONIUM CHLORIDE 1 mg/1 mL
INACTIVE INGREDIENTS: WATER; CETRIMONIUM CHLORIDE; LAURTRIMONIUM CHLORIDE; DIHYDROXYETHYL COCAMINE OXIDE; GLYCERETH-17 COCOATE; CITRIC ACID MONOHYDRATE

Drug Facts

Active ingredient

Benzalkonium Chloride 0.1%

Purpose

Antimicrobial

Uses

For hand sanitizing to decrease bacteria on the skin

Recommended for repeated use

Warnings

For external use only

When using this product avoid contact with eyes.

In case of eye contact, flush eyes with water.

Stop use and ask a doctor if irritation or redness develops, or if condition persists for more than 72 hours.

Keep out of reach of children.

If swallowed get medical help or contact a Poison Control Center right away.

Directions

Wash hands with soap and water

Rinse with potable water

Pump a small amount of foam into palm of hand

Rub thoroughly over all surfaces of both hands

Rub hands together briskly until dry

Inactive ingredients

Water, cetrimonium chloride, laurtrimonium chloride, dihydroxyethyl cocamine oxide, glycereth-17 cocoate, citric acid

PACKAGE LABEL

4 SURE Plus E3 Instant Foam Hand Sanitizer

Hand Sanitizer

Alcohol Free

Kills up to 99.9%

of germs on Hands

Refreshing and Soft on Skin

Acceptable for use in food processing facilities

NSF

Nonfood Compounds

Program Listed E3

#147444

550 mL (18.6 fl. oz) Made in the U.S.A.